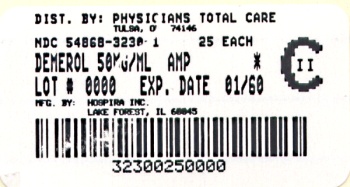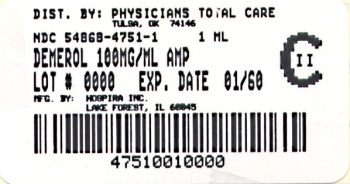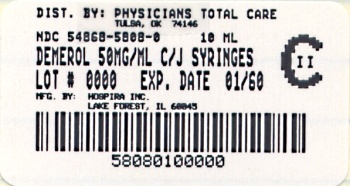 DRUG LABEL: DEMEROL
NDC: 54868-5808 | Form: INJECTION, SOLUTION
Manufacturer: Physicians Total Care, Inc.
Category: prescription | Type: Human prescription drug label
Date: 20111228
DEA Schedule: CII

ACTIVE INGREDIENTS: MEPERIDINE HYDROCHLORIDE 50 mg/1 mL
INACTIVE INGREDIENTS: SODIUM HYDROXIDE; HYDROCHLORIC ACID

Demerol™

meperidine hydrochloride injection, USP

CII

Rx only

DESCRIPTION

Meperidine hydrochloride is ethyl 1-methyl-4-phenylisonipecotate hydrochloride, a white crystalline substance with a melting point of 186°C to 189°C. It is readily soluble in water and has a neutral reaction and a slightly bitter taste. The solution is not decomposed by a short period of boiling.

DEMEROL injectable is supplied in Carpuject™ with luer lock of 2.5% (25 mg/1 mL), 5% (50 mg/1 mL), 7.5% (75 mg/1 mL), and 10% (100 mg/1 mL). Uni-Amp™ unit dose pak-ampuls of 5% solution (25 mg/0.5 mL), (50 mg/1 mL), (75 mg/1.5 mL), (100 mg/2 mL), and 10% solution (100 mg/1 mL). Multiple-dose vials of 5% and 10% solutions contain metacresol 0.1% as preservative.

The pH of DEMEROL solutions is adjusted between 3.5 and 6 with sodium hydroxide or hydrochloric acid.

DEMEROL, brand of meperidine hydrochloride, 5 percent solution has a specific gravity of 1.0086 at 20°C and 10 percent solution, a specific gravity of 1.0165 at 20°C.

CLINICAL PHARMACOLOGY

Meperidine hydrochloride is a narcotic analgesic with multiple actions qualitatively similar to those of morphine; the most prominent of these involve the central nervous system and organs composed of smooth muscle. The principal actions of therapeutic value are analgesia and sedation.

There is some evidence which suggests that meperidine may produce less smooth muscle spasm, constipation, and depression of the cough reflex than equianalgesic doses of morphine. Meperidine, in 60 mg to 80 mg parenteral doses, is approximately equivalent in analgesic effect to 10 mg of morphine. The onset of action is slightly more rapid than with morphine, and the duration of action is slightly shorter. Meperidine is significantly less effective by the oral than by the parenteral route, but the exact ratio of oral to parenteral effectiveness is unknown.

In clinical studies reported in the literature, changes in several pharmacokinetic parameters with increasing age have been observed. The initial volume of distribution and steady-state volume of distribution may be higher in elderly patients than in younger patients. The free fraction of meperidine in plasma may be higher in patients over 45 years of age than in younger patients.

INDICATIONS AND USAGE

For the relief of moderate to severe pain

For preoperative medication

For support of anesthesia

For obstetrical analgesia

CONTRAINDICATIONS

Hypersensitivity to meperidine.

Meperidine is contraindicated in patients who are receiving monoamine oxidase (MAO) inhibitors or those who have recently received such agents. Therapeutic doses of meperidine have occasionally precipitated unpredictable, severe, and occasionally fatal reactions in patients who have received such agents within 14 days. The mechanism of these reactions is unclear, but may be related to a preexisting hyperphenylalaninemia. Some have been characterized by coma, severe respiratory depression, cyanosis, and hypotension, and have resembled the syndrome of acute narcotic overdose. In other reactions the predominant manifestations have been hyperexcitability, convulsions, tachycardia, hyperpyrexia, and hypertension. Although it is not known that other narcotics are free of the risk of such reactions, virtually all of the reported reactions have occurred with meperidine. If a narcotic is needed in such patients, a sensitivity test should be performed in which repeated, small, incremental doses of morphine are administered over the course of several hours while the patient’s condition and vital signs are under careful observation. (Intravenous hydrocortisone or prednisolone have been used to treat severe reactions, with the addition of intravenous chlorpromazine in those cases exhibiting hypertension and hyperpyrexia. The usefulness and safety of narcotic antagonists in the treatment of these reactions is unknown.)

Solutions of DEMEROL and barbiturates are chemically incompatible.

WARNINGS

Drug Dependence. Meperidine can produce drug dependence of the morphine type and therefore has the potential for being abused. Psychic dependence, physical dependence, and tolerance may develop upon repeated administration of meperidine, and it should be prescribed and administered with the same degree of caution appropriate to the use of morphine. Like other narcotics, meperidine is subject to the provisions of the Federal narcotic laws.

Interaction with Other Central Nervous System Depressants. MEPERIDINE SHOULD BE USED WITH GREAT CAUTION AND IN REDUCED DOSAGE IN PATIENTS WHO ARE CONCURRENTLY RECEIVING OTHER NARCOTIC ANALGESICS, GENERAL ANESTHETICS, PHENOTHIAZINES, OTHER TRANQUILIZERS (SEE DOSAGE AND ADMINISTRATION), SEDATIVE-HYPNOTICS (INCLUDING BARBITURATES), TRICYCLIC ANTIDEPRESSANTS AND OTHER CNS DEPRESSANTS (INCLUDING ALCOHOL). RESPIRATORY DEPRESSION, HYPOTENSION, AND PROFOUND SEDATION OR COMA MAY RESULT.

Head Injury and Increased Intracranial Pressure. The respiratory depressant effects of meperidine and its capacity to elevate cerebrospinal fluid pressure may be markedly exaggerated in the presence of head injury, other intracranial lesions, or a preexisting increase in intracranial pressure. Furthermore, narcotics produce adverse reactions which may obscure the clinical course of patients with head injuries. In such patients, meperidine must be used with extreme caution and only if its use is deemed essential.

Intravenous Use. If necessary, meperidine may be given intravenously, but the injection should be given very slowly, preferably in the form of a diluted solution. Rapid intravenous injection of narcotic analgesics, including meperidine, increases the incidence of adverse reactions; severe respiratory depression, apnea, hypotension, peripheral circulatory collapse, and cardiac arrest have occurred. Meperidine should not be administered intravenously unless a narcotic antagonist and the facilities for assisted or controlled respiration are immediately available. When meperidine is given parenterally, especially intravenously, the patient should be lying down.

Asthma and Other Respiratory Conditions. Meperidine should be used with extreme caution in patients having an acute asthmatic attack, patients with chronic obstructive pulmonary disease or cor pulmonale, patients having a substantially decreased respiratory reserve, and patients with preexisting respiratory depression, hypoxia, or hypercapnia. In such patients, even usual therapeutic doses of narcotics may decrease respiratory drive while simultaneously increasing airway resistance to the point of apnea.

Hypotensive Effect. The administration of meperidine may result in severe hypotension in the postoperative patient or any individual whose ability to maintain blood pressure has been compromised by a depleted blood volume or the administration of drugs such as the phenothiazines or certain anesthetics.

Usage in Ambulatory Patients. Meperidine may impair the mental and/or physical abilities required for the performance of potentially hazardous tasks such as driving a car or operating machinery. The patient should be cautioned accordingly.

Meperidine, like other narcotics, may produce orthostatic hypotension in ambulatory patients.

Usage in Pregnancy and Lactation. Meperidine should not be used in pregnant women prior to the labor period, unless in the judgment of the physician the potential benefits outweigh the possible hazards, because safe use in pregnancy prior to labor has not been established relative to possible adverse effects on fetal development.

When used as an obstetrical analgesic, meperidine crosses the placental barrier and can produce depression of respiration and psychophysiologic functions in the newborn. Resuscitation may be required (see OVERDOSAGE).

Meperidine appears in the milk of nursing mothers receiving the drug.

PRECAUTIONS

As with all intramuscular preparations, DEMEROL intramuscular injection should be injected well within the body of a large muscle.

Supraventricular Tachycardias. Meperidine should be used with caution in patients with atrial flutter and other supraventricular tachycardias because of a possible vagolytic action which may produce a significant increase in the ventricular response rate.

Convulsions. Meperidine may aggravate preexisting convulsions in patients with convulsive disorders. If dosage is escalated substantially above recommended levels because of tolerance development, convulsions may occur in individuals without a history of convulsive disorders.

Acute Abdominal Conditions. The administration of meperidine or other narcotics may obscure the diagnosis or clinical course in patients with acute abdominal conditions.

Special Risk Patients. Meperidine should be given with caution and the initial dose should be reduced in certain patients such as the debilitated, and those with severe impairment of hepatic or renal function, hypothyroidism, Addison’s disease, and prostatic hypertrophy or urethral stricture.

GERIATRIC USE

Geriatric Use. Clinical studies of DEMEROL did not include sufficient numbers of subjects aged 65 and over to determine whether they respond differently from younger subjects. Other reported clinical experience has not identified differences in response between the elderly and younger patients. In general, dose selection for an elderly patient should be low, usually starting at the low end of the dosing range, reflecting the greater frequency of decreased hepatic, renal, or cardiac function, and of concomitant disease or other drug therapy. (See DOSAGE AND ADMINISTRATION.)

Sedating drugs may cause confusion and oversedation in the elderly; elderly patients generally should be started on low doses of DEMEROL and observed closely.

This drug is known to be excreted by the kidney, and the risk of toxic reactions to this drug may be greater in patients with impaired renal function. Because elderly patients are more likely to have decreased renal function, care should be taken in dose selection, and it may be useful to monitor renal function.

Clinical studies indicate that differences in various pharmacokinetic parameters may exist between elderly and younger patients. (See CLINICAL PHARMACOLOGY.)

ADVERSE REACTIONS

The major hazards of meperidine, as with other narcotic analgesics, are respiratory depression and, to a lesser degree, circulatory depression; respiratory arrest, shock, and cardiac arrest have occurred.

The most frequently observed adverse reactions include lightheadedness, dizziness, sedation, nausea, vomiting, and sweating. These effects seem to be more prominent in ambulatory patients and in those who are not experiencing severe pain. In such individuals, lower doses are advisable. Some adverse reactions in ambulatory patients may be alleviated if the patient lies down.

Other adverse reactions include:

Nervous System. Euphoria, dysphoria, weakness, headache, agitation, tremor, uncoordinated muscle movements, severe convulsions, transient hallucinations and disorientation, visual disturbances. Inadvertent injection about a nerve trunk may result in sensory-motor paralysis which is usually, though not always, transitory.

Gastrointestinal. Dry mouth, constipation, biliary tract spasm.

Cardiovascular. Flushing of the face, tachycardia, bradycardia, palpitation, hypotension (see WARNINGS), syncope, phlebitis following intravenous injection.

Genitourinary. Urinary retention.

Allergic. Pruritus, urticaria, other skin rashes, wheal and flare over the vein with intravenous injection.

Other. Pain at injection site; local tissue irritation and induration following subcutaneous injection, particularly when repeated; antidiuretic effect.

OVERDOSAGE

Symptoms. Serious overdosage with meperidine is characterized by respiratory depression (a decrease in respiratory rate and/or tidal volume, Cheyne-Stokes respiration, cyanosis), extreme somnolence progressing to stupor or coma, skeletal muscle flaccidity, cold and clammy skin, and sometimes bradycardia and hypotension. In severe overdosage, particularly by the intravenous route, apnea, circulatory collapse, cardiac arrest, and death may occur.

Treatment. Primary attention should be given to the reestablishment of adequate respiratory exchange through provision of a patent airway and institution of assisted or controlled ventilation. The narcotic antagonist, naloxone hydrochloride, is a specific antidote against respiratory depression which may result from overdosage or unusual sensitivity to narcotics, including meperidine. Therefore, an appropriate dose of this antagonist should be administered, preferably by the intravenous route, simultaneously with efforts at respiratory resuscitation.

An antagonist should not be administered in the absence of clinically significant respiratory or cardiovascular depression.

Oxygen, intravenous fluids, vasopressors, and other supportive measures should be employed as indicated.

NOTE: In an individual physically dependent on narcotics, the administration of the usual dose of a narcotic antagonist will precipitate an acute withdrawal syndrome. The severity of this syndrome will depend on the degree of physical dependence and the dose of antagonist administered. The use of narcotic antagonists in such individuals should be avoided if possible. If a narcotic antagonist must be used to treat serious respiratory depression in the physically dependent patient, the antagonist should be administered with extreme care and only one-fifth to one-tenth the usual initial dose administered.

DOSAGE AND ADMINISTRATION

For Relief of Pain

Dosage should be adjusted according to the severity of the pain and the response of the patient. While subcutaneous administration is suitable for occasional use, intramuscular administration is preferred when repeated doses are required. If intravenous administration is required, dosage should be decreased and the injection made very slowly, preferably utilizing a diluted solution. The dose of DEMEROL should be proportionately reduced (usually by 25 to 50 percent) when administered concomitantly with phenothiazines and many other tranquilizers since they potentiate the action of DEMEROL.

Adults. The usual dosage is 50 mg to 150 mg intramuscularly or subcutaneously every 3 or 4 hours as necessary. Elderly patients should usually be given meperidine at the lower end of the dose range and observed closely.

Children. The usual dosage is 0.5 mg/lb to 0.8 mg/lb intramuscularly or subcutaneously up to the adult dose, every 3 or 4 hours as necessary.

For Preoperative Medication

Adults. The usual dosage is 50 mg to 100 mg intramuscularly or subcutaneously, 30 to 90 minutes before the beginning of anesthesia. Elderly patients should usually be given meperidine at the lower end of the dose range and observed closely.

Children. The usual dosage is 0.5 mg/lb to 1 mg/lb intramuscularly or subcutaneously up to the adult dose, 30 to 90 minutes before the beginning of anesthesia.

For Support of Anesthesia

Repeated slow intravenous injections of fractional doses (e.g., 10 mg/mL) or continuous intravenous infusion of a more dilute solution (e.g., 1 mg/mL) should be used. The dose should be titrated to the needs of the patient and will depend on the premedication and type of anesthesia being employed, the characteristics of the particular patient, and the nature and duration of the operative procedure. Elderly patients should usually be given meperidine at the lower end of the dose range and observed closely.

For Obstetrical Analgesia

The usual dosage is 50 mg to 100 mg intramuscularly or subcutaneously when pain becomes regular, and may be repeated at 1- to 3-hour intervals.

Parenteral drug products should be inspected visually for particulate and discoloration prior to administration whenever solution and container permit.

HOW SUPPLIED

For Parenteral Use

Solutions of DEMEROL for parenteral use are clear and colorless and are available as follows:

NDC Number | Container | Concentration | Fill (mL) | Quantity
54868-5808-0 | Carpuject with luer lock | 5% (50 mg/mL) | 1 | 10
54868-3230-1 | Uni-Amp unit dose pak | 5% (50 mg) | 1 | 25
54868-4751-0 | Uni-Amp unit dose pak | 10% (100 mg) | 1 | 25
54868-4751-1 | Uni-Amp unit dose pak | 10% (100 mg) | 1 | 1

Carpuject™ are packaged in a Slim-Pak™ tamper detection package. To prevent needle-stick injuries, needles should not be recapped, purposely bent, or broken by hand. Blunt cannulas should not be recapped, purposely bent or broken by hand.

NOTE: The pH of DEMEROL solutions is adjusted between 3.5 and 6 with sodium hydroxide or hydrochloric acid. Multiple-dose vials contain metacresol 0.1 percent as preservative. No preservatives are added to the ampuls or Carpuject™ sterile cartridge units.

Store at 20 to 25°C (68 to 77°F). [See USP Controlled Room Temperature.]

Demerol is not a trademark of Hospira.

Revised: June, 2010

Printed in USA EN-2526

Hospira, Inc., Lake Forest, IL 60045

Additional bar code label applied by:
Physicians Total Care, Inc.
Tulsa, Oklahoma 74146